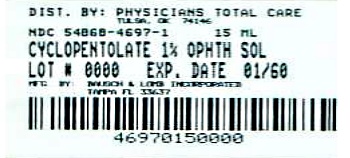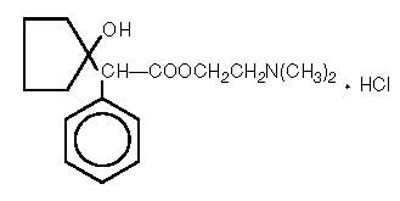 DRUG LABEL: Cyclopentolate Hydrochloride
NDC: 54868-4697 | Form: SOLUTION/ DROPS
Manufacturer: Physicians Total Care, Inc.
Category: prescription | Type: HUMAN PRESCRIPTION DRUG LABEL
Date: 20130206

ACTIVE INGREDIENTS: CYCLOPENTOLATE HYDROCHLORIDE 10 mg/1 mL
INACTIVE INGREDIENTS: BENZALKONIUM CHLORIDE; BORIC ACID; EDETATE DISODIUM; HYDROCHLORIC ACID; POTASSIUM CHLORIDE; WATER; SODIUM CARBONATE

Cyclopentolate Hydrochloride
Ophthalmic Solution USP, 1%
(Sterile)

Rx only

DESCRIPTION:

Cyclopentolate Hydrochloride Ophthalmic Solution USP, 1% is an anticholinergic prepared as a sterile, borate buffered, solution for topical ocular use. The active ingredient is represented by the following structural formula:

C17H25NO3 • HCl
Mol. Wt. 327.85

Chemical name: 2-(Dimethylamino) ethyl 1-hydroxy-α-phenylcyclopentaneacetate hydrochloride.

Each mL Contains:

ACTIVE: Cyclopentolate Hydrochloride, 10 mg (1%)

INACTIVES: Boric Acid, Potassium Chloride, Edetate Disodium, Purified Water. Sodium Carbonate and/or Hydrochloric Acid may be added to adjust pH (3.0-5.5).

PRESERVATIVE ADDED: Benzalkonium Chloride 0.01%.

CLINICAL PHARMACOLOGY:

This anticholinergic preparation blocks the responses of the sphincter muscle of the iris and the accommodative muscle of the ciliary body to cholinergic stimulation, producing pupillary dilation (mydriasis) and paralysis of accommodation (cycloplegia). It acts rapidly, but has a shorter duration than atropine. Maximal cycloplegia occurs within 25 to 75 minutes after instillation. Complete recovery of accommodation usually takes 6 to 24 hours. Complete recovery from mydriasis in some individuals may require several days.

INDICATIONS AND USAGE:

Cyclopentolate Hydrochloride Ophthalmic Solution is used to produce mydriasis and cycloplegia in diagnostic procedures.

CONTRAINDICATIONS:

Should not be used when narrow-angle glaucoma or anatomical narrow angles are present, or where there is hypersensitivity to any component of this preparation.

WARNINGS:

For Topical Use Only - Not For Injection. This preparation may cause CNS disturbances. This is especially true in younger age groups, but may occur at any age, especially with the stronger cyclopentolate hydrochloride solution. Premature and small infants are especially prone to CNS and cardiopulmonary side effects from systemic absorption of cyclopentolate. To minimize absorption, use only 1 drop of a 0.5% solution per eye followed by pressure applied over the nasolacrimal sac for two to three minutes. Observe infants closely for at least 30 minutes following instillation.

PRECAUTIONS:

General:

To avoid inducing angle closure glaucoma, an estimation of the depth of the angle of the anterior chamber should be made. The lacrimal sac should be compressed by digital pressure for two to three minutes after instillation to avoid excessive systemic absorption. Caution should be observed when considering use of this medication in the presence of Down’s syndrome or mongolism, and in those predisposed to angle-closure glaucoma.

Information for Patients:

Do not touch dropper tip to any surface as this may contaminate the solution. A transient burning sensation may occur upon instillation. Patients should be advised not to drive or engage in other hazardous activities while pupils are dilated. Patients may experience sensitivity to light and should protect eyes in bright illumination during dilation. Parents should be warned not to get this preparation in their child’s mouth and to wash their own hands and the child’s hands following administration.

Drug Interactions:

Cyclopentolate may interfere with the antiglaucoma action of carbachol or pilocarpine; also, concurrent use of these medications may antagonize the anti-glaucoma and miotic actions of ophthalmic cholinesterase inhibitors.

Carcinogenesis, Mutagenesis, Impairment of Fertility:

Studies in animals or humans have not been conducted to evaluate the potential of these effects.

Pregnancy Category C:

Animal reproduction studies have not been conducted with cyclopentolate. It is also not known whether cyclopentolate can cause fetal harm when administered to a pregnant woman or can affect reproduction capacity. Cyclopentolate should be administered to a pregnant woman only if clearly needed.

Nursing Mothers:

It is not known whether this drug is excreted in human milk. Because many drugs are excreted in human milk, caution should be exercised when cyclopentolate hydrochloride is administered to a nursing woman.

Pediatric Use:

Increased susceptibility to cyclopentolate has been reported in pediatric patients with spastic paralysis or brain damage. Therefore, cyclopentolate should be used with great caution in these patients. Feeding intolerance may follow ophthalmic use of this product in neonates. It is recommended that feeding be withheld for four (4) hours after examination. Do not use concentrations higher than 0.5% in small infants (see WARNINGS).

Geriatric Use:

In the elderly and others where increased intraocular pressure may be encountered, mydriatics and cycloplegics should be used cautiously.

ADVERSE REACTIONS:

Ocular: Increased intraocular pressure, burning, photophobia, blurred vision, irritation, hyperemia, conjunctivitis, blepharoconjunctivitis, punctate keratitis, synechiae.

Systemic: Use of cyclopentolate has been associated with psychotic reactions and behavioral disturbances, usually in pediatric patients, especially with a 2% concentration. These disturbances include ataxia, incoherent speech, restlessness, hallucinations, hyperactivity, seizures, disorientation as to time and place, and failure to recognize people. This drug produces reactions similar to those of other anticholinergic drugs, but the central nervous system manifestations as noted above are more common. Other toxic manifestations of anticholinergic drugs are skin rash, abdominal distention in infants, unusual drowsiness, tachycardia, hyperpyrexia, vasodilation, urinary retention, diminished gastrointestinal motility and decreased secretion in salivary and sweat glands, pharynx, bronchi and nasal passages. Severe manifestations of toxicity include coma, medullary paralysis and death.

OVERDOSAGE:

Excessive dosage may produce exaggerated symptoms as noted in ADVERSE REACTIONS. When administration of the drug product is discontinued, the patient usually recovers spontaneously. In case of severe manifestations of toxicity the antidote of choice is physostigmine salicylate.

Pediatric Dose: As an antidote, slowly inject intravenously 0.5 mg physostigmine salicylate. If toxic symptoms persist and no cholinergic symptoms are produced repeat at five minute intervals to a maximum cumulative dose of 2 mg.

Adolescent and Adult: As an antidote, slowly inject 2 mg physostigmine salicylate intravenously. A second dose of 1 to 2 mg may be given after 20 minutes if no reversal of toxic manifestations has occurred. ^(1, 2, 3)

DOSAGE AND ADMINISTRATION:

Adults: One or two drops of 0.5%, 1% or 2% solution in the eye, which may be repeated in five to ten minutes if necessary. Complete recovery usually occurs in 24 hours.

Pediatric Patients: One or two drops of 0.5%, 1% or 2% solution in the eye, which may be repeated five to ten minutes later by a second application of 0.5% or 1% solution if necessary.

Small Infants: A single instillation of one drop of 0.5% solution in the eye. To minimize absorption, apply pressure over the nasolacrimal sac for two to three minutes. Observe infant closely for at least 30 minutes following instillation.

Individuals with heavily pigmented irises may require higher strengths.

HOW SUPPLIED:

Cyclopentolate Hydrochloride Ophthalmic Solution USP, 1% is available in multidose plastic squeeze bottles with a controlled drop tip and red cap in the following sizes:

15 mL bottle - Prod. No. 04911 NDC 54868-4697-1

Storage:

Store between 15°-30°C (59°-86°F).

FOR OPHTHALMIC USE ONLY

DO NOT USE IF IMPRINTED NECKBAND IS NOT INTACT.

KEEP OUT OF REACH OF CHILDREN.

REFERENCES

1. Rumack, B.H.: Anticholinergic Poisoning: Treatment with Physostigmine. Pediatrics 52(6): 449-51, 1973.

2. Duvoisin, R.C. and Katz, R.: Reversal of Central Anticholinergic Syndromes in Man by Physostigmine, J. Am. Med. Assn. 206(9): 1963-65,1968.

3. Grant, W.M.: Toxicology of the Eye. Second Edition, Volume 1. Springfield, Illinois, Charles C. Thomas: 1974.

Revised November 2007

Bausch & Lomb Incorporated

Tampa, FL 33637

©Bausch & Lomb Incorporated

9114600 (Folded)

9114700 (Flat)

Distributed by:
Physicians Total Care, Inc.
Tulsa, OK 74146

PACKAGE/LABEL PRINCIPAL DISPLAY PANEL

NDC 54868-4697-1

Cyclopentolate Hydrochloride Ophthalmic Solution USP, 1% (Sterile)

Rx only

[icon- eye] [icon- 1%] [icon- solution] [icon- 15 mL]